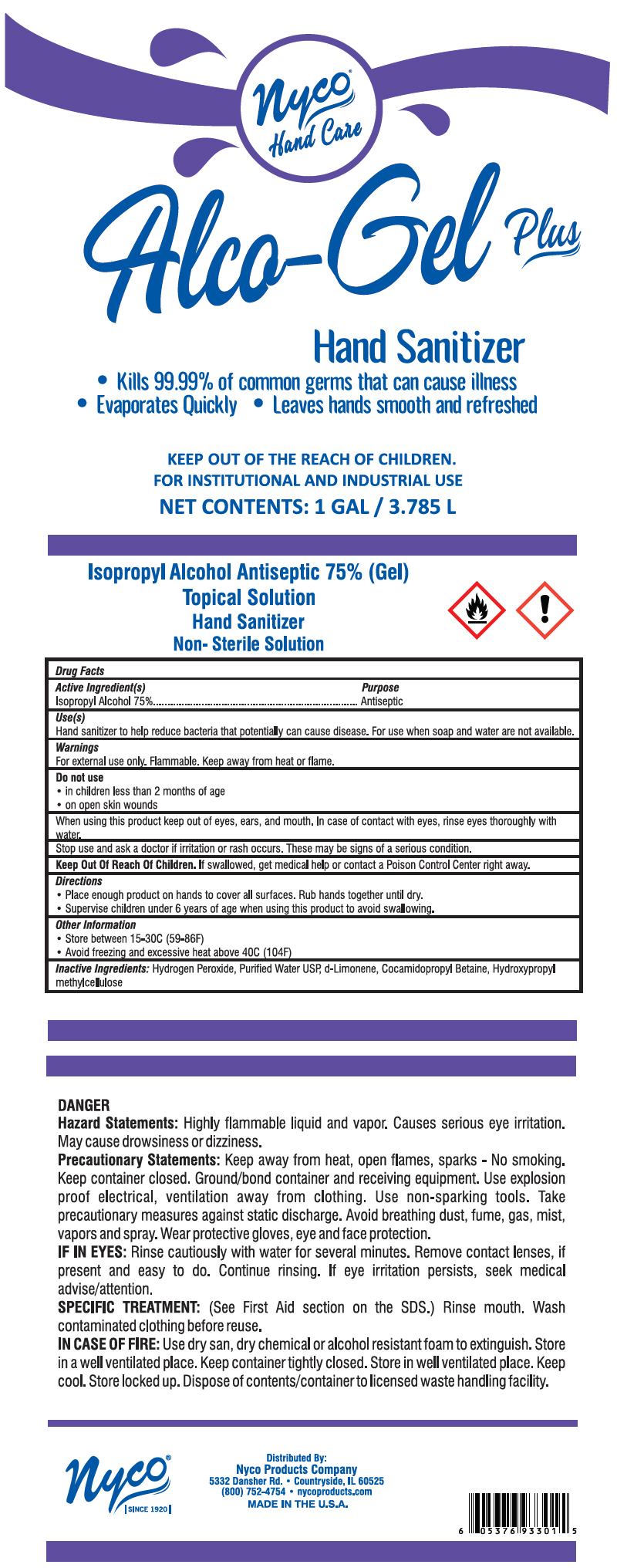 DRUG LABEL: Alco-Gel
NDC: 54555-131 | Form: GEL
Manufacturer: Brainerd Chemical Company Inc.,
Category: otc | Type: HUMAN OTC DRUG LABEL
Date: 20200630

ACTIVE INGREDIENTS: alcohol 750 mL/1 L
INACTIVE INGREDIENTS: Cocamidopropyl Betaine; hydrogen peroxide; water; LIMONENE OXIDE, TRANS-(+)-; HYDROXYMETHYL CELLULOSE

Alco-Gel

Drug Facts

Active ingredient[s]

Isopropyl alcohol 75% v/v

Purpose

Antiseptic

Use(s)

Hand sanitizer to help reduce bacteria that potentially can cause disease. For use when soap and water are not available.

Warnings

For external use only. Flammable. Keep away from heat or flame

Do not use

- in children less than 2 months of age
- on open skin wounds

When using this product keep out of eyes, ears, and mouth. In case of contact with eyes, rinse eyes thoroughly with water.

Stop use and ask a doctor if irritation or rash occurs. These may be signs of a serious condition.

Keep out of reach of children. If swallowed, get medical help or contact a Poison Control Center right away.

Directions

- Place enough product on hands to cover all surfaces. Rub hands together until dry.
- Supervise children under 6 years of age when using this product to avoid swallowing.

Other information

- Store between 15-30C (59-86F)
- Avoid freezing and excessive heat above 40C (104F)

Inactive ingredients

hydrogen peroxide, purified water USP, d-limonene, cocamidopropyl betaine, hydroxypropyl methylcellulose

Distributed By:
Nyco Products Company
5332 Dansher Rd. • Countryside, IL 60525

PRINCIPAL DISPLAY PANEL - 3.785 L Jug Label

Nyco®
Hand Care

Alco-Gel Plus

Hand Sanitizer

• Kills 99.99% of common germs that can cause illness
• Evaporates Quickly • Leaves hands smooth and refreshed

KEEP OUT OF THE REACH OF CHILDREN.
FOR INSTITUTIONAL AND INDUSTRIAL USE

NET CONTENTS: 1 GAL / 3.785 L